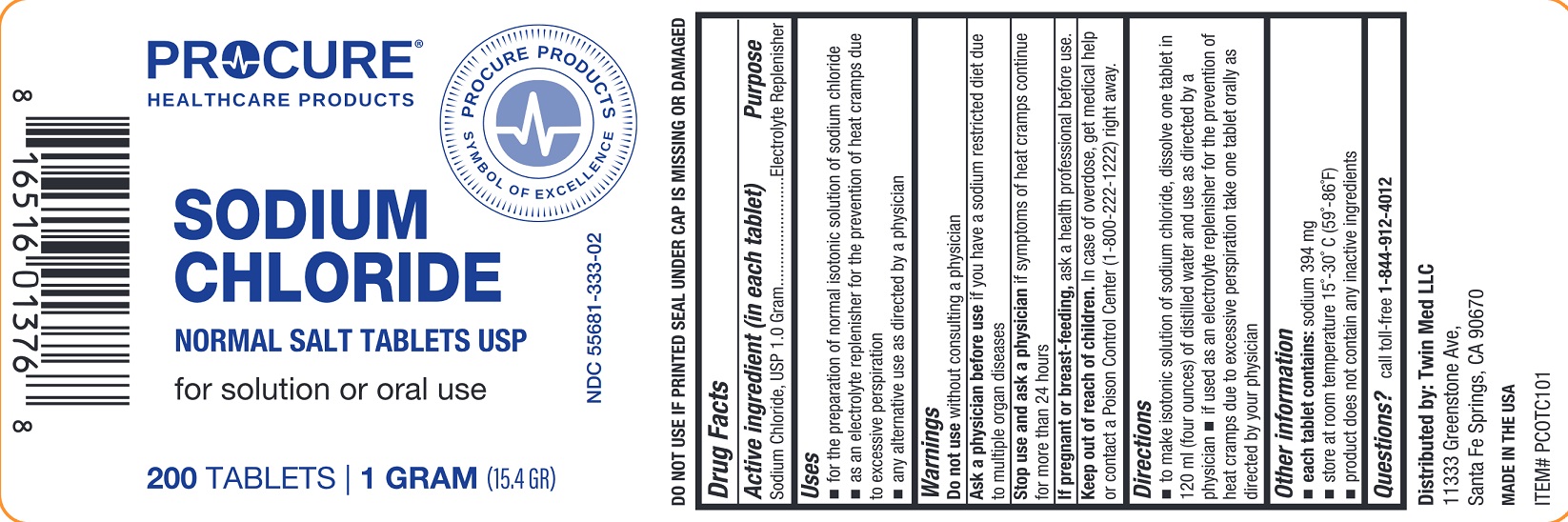 DRUG LABEL: Sodium Chloride

NDC: 55681-333 | Form: TABLET
Manufacturer: TWIN MED LLC
Category: otc | Type: HUMAN OTC DRUG LABEL
Date: 20250703

ACTIVE INGREDIENTS: SODIUM CHLORIDE 1 g/1 1

Sodium Chloride Tablets, USP

Drug Facts

Active ingredient (in each tablet)

Sodium Chloride, USP 1.0 Gram

Purpose

Electrolyte Replenisher

Uses

- for the preparation of normal isotonic solution of sodium chloride
- as an electrolyte replenisher for the prevention of heat cramps due to excessive perspiration
- any alternative use as directed by a physician

Warnings

Do not usewithout consulting a physician

ASK DOCTOR

Ask a physician before useif you have a sodium restricted diet due to multiple organ diseases

Stop use and ask a physician ifsymptoms of heat cramps continue for more than 24 hours.

PREGNANCY OR BREAST FEEDING

If pregnant or breast-feeding,ask a health professional before use.

Keep out of reach of children.

In case of overdose, get medical help or contact a Poison Control Center (1-800-222-1222) right away.

Directions

- to make isontonic solution of sodium chloride, dissolve one tablet in 120 ml (four ounces) of distilled water and use as directed by a physician.
- if used as an electrolyte replenisher for the prevention of heat cramps due to excessive perspiration take one tablet orally as directed by your physician.

Inactive Ingredient

None

Other information:

- each tablet contains:sodium 394 mg
- store at room temperature 15°-30°C (59°-86°F)
- product does not contain any inactive ingredients

Questions or comments?

call toll-free 1-844-912-4012

DO NOT USE IF PRINTED SAFETY SEAL UNDER CAP IS BROKEN OR DAMAGED

Distributed by:

Twin Med LLC

11333 Greenstone Ave,

Santa Fe Springs, CA 90670

MADE IN THE USA